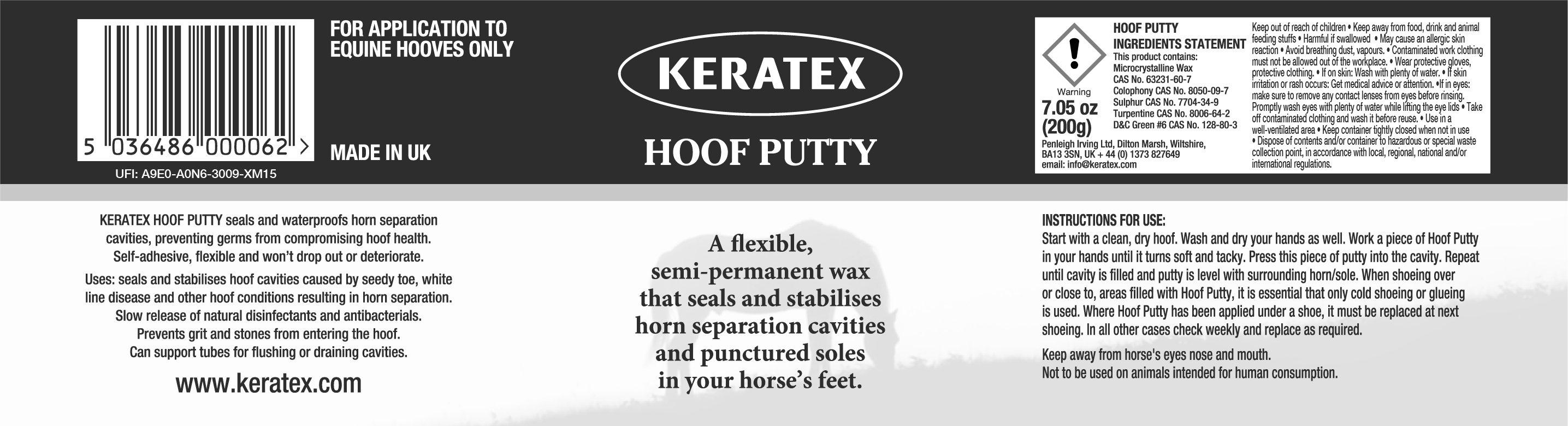 DRUG LABEL: Keratex
NDC: 27426-070 | Form: PASTE
Manufacturer: Penleigh Irving Ltd
Category: animal | Type: OTC ANIMAL DRUG LABEL
Date: 20250507

ACTIVE INGREDIENTS: MICROCRYSTALLINE WAX 103.31 g/147 g; ROSIN 35.11 g/147 g; TURPENTINE 7.11 g/147 g; SULFUR 1.44 g/147 g

Keep out of reach of children. Keep away from food, drink and animal feeding stuffs. Harmful if swallowed. May cause an allergic skin reaction. Avoid breathing dust, vapours. Contaminated work clothing must not be allowed out of the workplace. Wear protective gloves, protective clothing. If on skin: Wash with plenty of soap and water. If skin irritation or rash occurs: Get medical advice or attention. If in eyes: make sure to remove any contact lenses from the eyes before rinsing. Promptly wash eyes with plenty of water while lifting the eye lids. Take off contaminated clothing and wash it before reuse. Use in a well-ventilated area. Keep container tightly closed when not in use. Dispose of contents and/or container to hazardous or special waste collection point, in accordance with local, regional, national and/or international regulations.

PACKAGE LABEL

Keratex Hoof Putty

A flexible, semi-permanent wax that seals and stabilises horn separation cavities and punctured soles in your horse’s feet.

Keratex Hoof Putty seals and waterproofs horn separation cavities, preventing germs from compromising hoof health. Self-adhesive, flexible and won’t drop out or deteriorate.

Uses: Seals and stabilises hoof cavities caused by seedy toe, white line disease and other hoof conditions resulting in horn separation. Slow release of natural disinfectants and antibacterials. Prevents grit and stones from entering the hoof. Can support tubes for flushing or draining cavities.

For Application to Equine Hooves Only

Made in UK

Instructions for Use: Start with a clean dry hoof. Wash and dry your hands as well. Work a piece of Hoof Putty in your hands until it turns soft and tacky. Press this piece of putty into the cavity. Repeat until cavity is filled and putty is level with surrounding horn/sole. When shoeing over or close to, areas filled with Hoof Putty, it is essential that only cold shoeing or glueing is used. Where Hoof Putty has been applied under a shoe, it must be replaced at next shoeing. In all other cases check weekly and replace as required.

Keep away from horse’s eyes, nose and mouth. Not to be used on animals intended for human consumption.

Hoof Putty Ingredients Statement. This product contains: Microcrystalline wax CAS No. 63231-60-7. Colophony CAS No. 8050-09-7. Sulphur CAS No. 7704-34-9. Turpentine CAS No. 8006-64-2. D&C Green #6 CAS No. 128-80-3.

7.05 oz (200g)

Penleigh Irving Ltd

Dilton Marsh, Wiltshire, BA13 3SN, UK

+44(0) 1373 827649

email: info@keratex.com

www.keratex.com

UFI: A9E0-AON6-3009-XM15